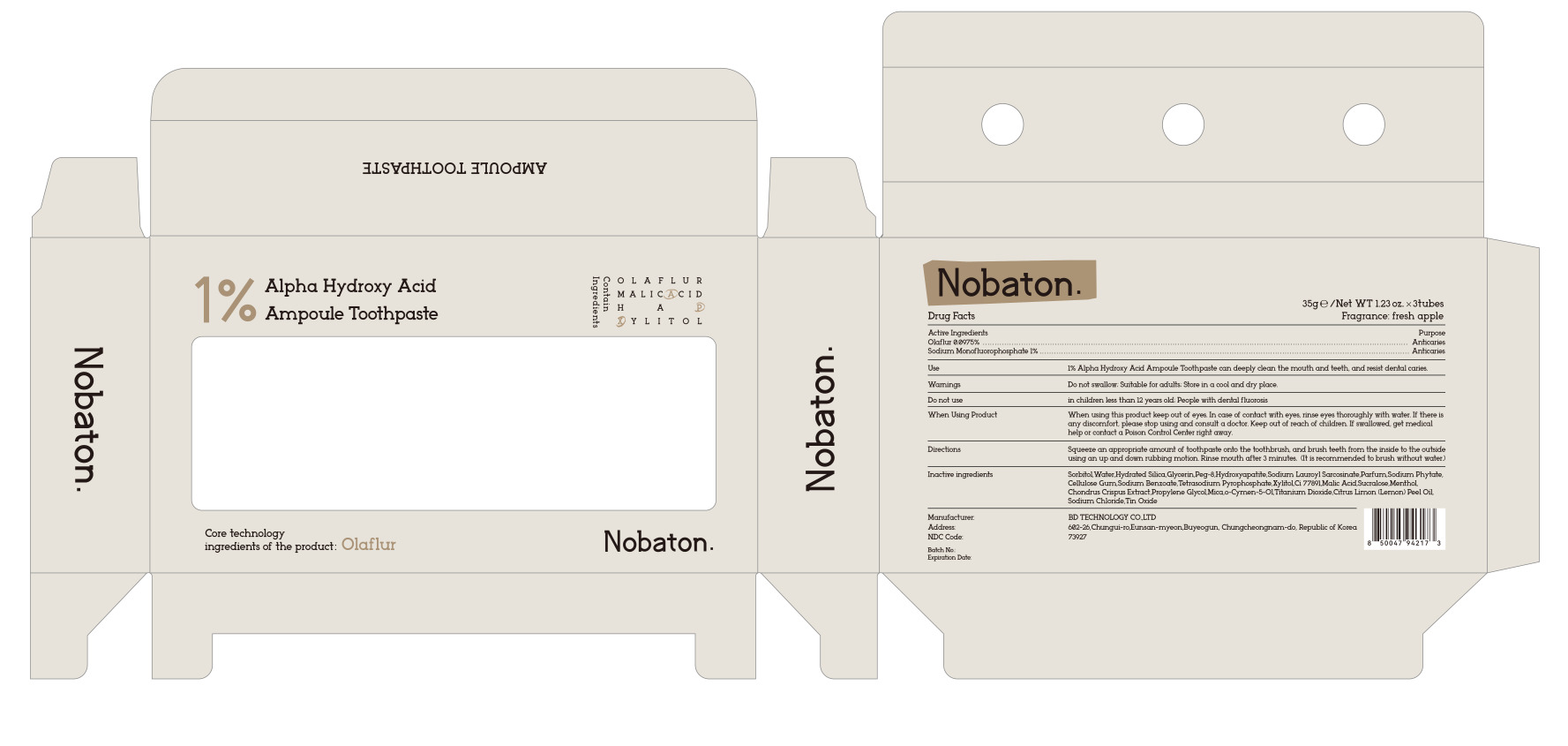 DRUG LABEL: Nobaton 1% Alpha Hydroxy Acid Ampoule
NDC: 73927-0008 | Form: OINTMENT
Manufacturer: BD TECHNOLOGY CO.,LTD
Category: otc | Type: HUMAN OTC DRUG LABEL
Date: 20250420

ACTIVE INGREDIENTS: SODIUM MONOFLUOROPHOSPHATE 1 g/100 g; OLAFLUR 0.0975 g/100 g
INACTIVE INGREDIENTS: TITANIUM; SUCRALOSE; MICA; CELLULOSE GUM; PROPYLENE GLYCOL; O-CYMEN-5-OL; MALIC ACID; CHONDRUS CRISPUS CARRAGEENAN; SODIUM BENZOATE; CITRUS LIMON (LEMON) PEEL OIL; SODIUM CHLORIDE; TETRASODIUM PYROPHOSPHATE; SORBITOL; WATER; HYDRATED SILICA; GLYCERIN; PEG-8; HYDROXYAPATITE; SODIUM LAUROYL SARCOSINATE; PARFUMIDINE; XYLITOL; CI 77891; SODIUM PHYTATE; MENTHOL; TIN OXIDE

73927-0008
Nobaton 1% Alpha Hydroxy Acid Ampoule Toothpaste

Active Ingredient(s)

OLAFLUR 0.0975%

SODIUM MONOFLUOROPHOSPHATE 1%

Purpose

Anticaries

Use

l% Alpha Hydroxy Acid Ampoule Toothpaste can deeply clean the mouth and teeth, and resist dental caries.

Warnings

Do not swallow; Suitable for adults; Store in a cool and dry place.

Do not use

in chilren less than 12 years old; People with dental fluorosis

When using this product keep out of eyes. In case of contact with eyes, rinse eyes thoroughly with water. If there is
any discomfort, please stop using and consult a doctor. Keep out of reach of children. If swallowed, get medical
help or contact a Poison Control Center right away.

STOP USE

In case of contact with eyes, rinse eyes thoroughly with water.

Keep out of reach of children.

Directions

Squeeze an appropriate amount of toothpaste onto the toothbrush, and brush teeth from the inside to the outside
using an up and down rubbing motion. Rinse mouth after 3 minutes. (It is recommended to brush without water)

Other information

No

Inactive ingredients

SorbitolWater,Hydrated Silica,Glycerin,Peg-8,Hydroxyapatite,Sodium Lauroyl Sarcosinate,Parfum,Sodium Phytate,
Cellulose Gum,Sodium Benzoate,Tetrasodium Pyrophosphate,Xyltol,Ci 77891Malic Acid,Sucralose,Menthol,
Chondrus Crispus Extract,Propylene GlycolMica,o-Cymen-5-OlTitanium Dioxide,Citrus Limon (Lemon) Peel Oil,
Sodium Chloride,Tin Oxide